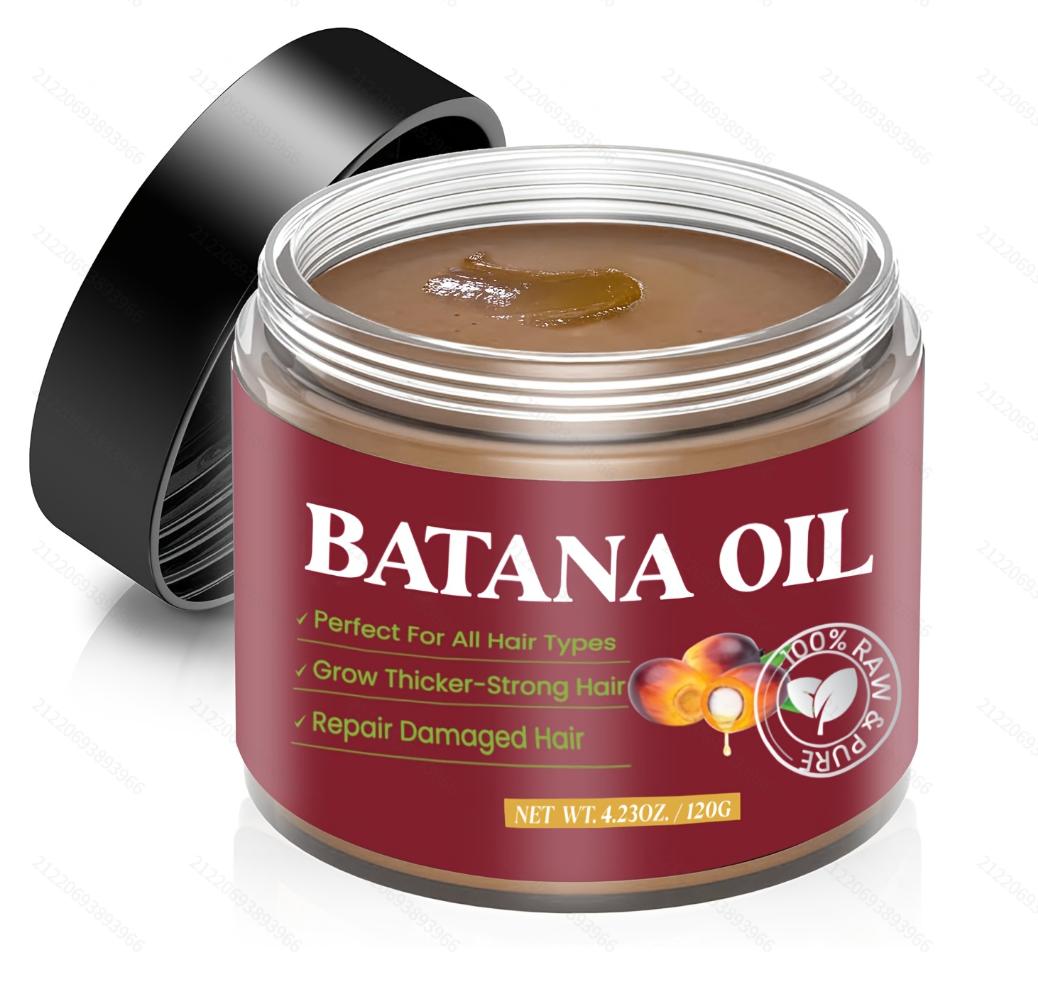 DRUG LABEL: SY Batana Hair Oil
NDC: 84778-036 | Form: CREAM
Manufacturer: Guangzhou Yixin Cross-border E-commerce Co., Ltd.
Category: otc | Type: HUMAN OTC DRUG LABEL
Date: 20241113

ACTIVE INGREDIENTS: BABASSU OIL 120 g/120 g
INACTIVE INGREDIENTS: WATER

COMPONENTS

Elaeis Oleifera Kernel Oil120g

PURPOSE

Deeply moisturizes dry and damaged hair to help restore softness and shine

INDICATIONS AND USAGE

It can help relieve dry and itchy scalp, reduce dandruff and keep the scalp healthy. Take an appropriate amount of SY Batana Hair Oil and apply it evenly on wet or dry hair, especially the ends of the hair. Gently massage the hair and scalp to promote absorption.

WARNINGS

For external use only.

If sensitive irritation occurs, please stop using and store in a cool and dry place.

DOSAGE AND ADMINISTRATION

For external use only.

DO NOT USE

Please make sure your skin is clean before use. Avoid using on open wounds or skin with allergic reactions.

WHEN USING

Apply an appropriate amount of SY Batana Hair Oil to your hair, especially to the ends or roots. Wrap your hair with a shower cap and leave it on for 30 minutes to an hour. Finally, wash it with warm water. It is suitable for dry, dull, and dull hair. It can provide deep moisture and restore the softness and luster of hair.

Do not use on open wounds or allergic skin.

KEEP OUT OF REACH OF CHILDREN

If sxralowed, get medical help or contact a Poison Conirol Cenler ngiht away.

INACTIVE INGREDIENT

water